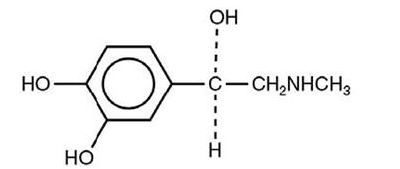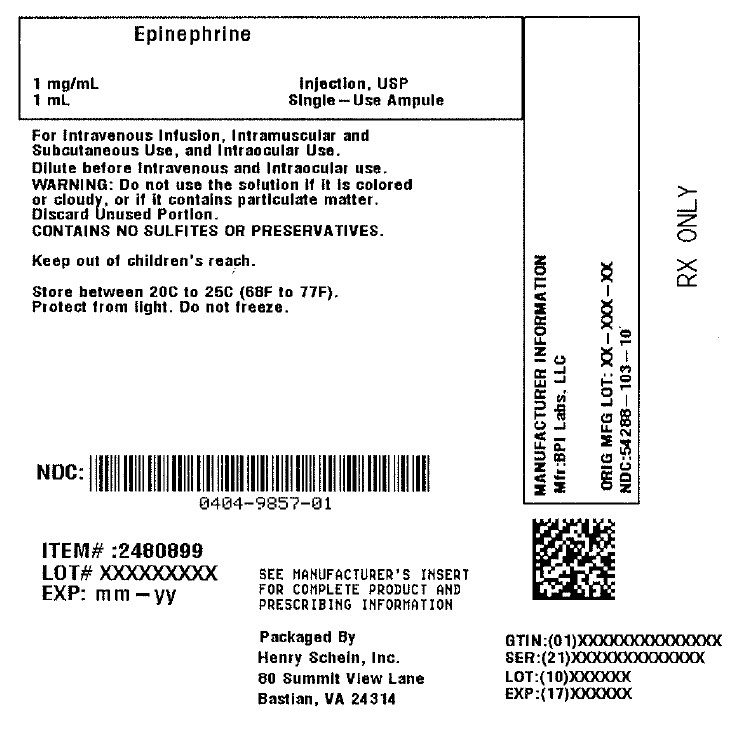 DRUG LABEL: EPINEPHRINE
NDC: 0404-9857 | Form: INJECTION, SOLUTION, CONCENTRATE
Manufacturer: Henry Schein, Inc.
Category: prescription | Type: HUMAN PRESCRIPTION DRUG LABEL
Date: 20260113

ACTIVE INGREDIENTS: EPINEPHRINE 1 mg/1 mL
INACTIVE INGREDIENTS: SODIUM CHLORIDE 9 mg/1 mL; HYDROCHLORIC ACID; WATER

HIGHLIGHTS OF PRESCRIBING INFORMATION

These highlights do not include all the information needed to use EPINEPHRINE INJECTION USP safely and effectively. See full prescribing information for EPINEPHRINE INJECTION USP.
EPINEPHRINE INJECTION USP, 1 mg/mL ampule, for intravenous, intramuscular, subcutaneous and intraocular use
Initial U.S. Approval: 1939

1 INDICATIONS AND USAGE

Epinephrine is a non-selective alpha and beta adrenergic agonist indicated:

- To increase mean arterial blood pressure in adult patients with hypotension associated with septic shock. (1.1)
- For emergency treatment of allergic reactions (Type 1), including anaphylaxis. (1.2)
- For induction and maintenance of mydriasis during intraocular surgery. (1.3)

2 DOSAGE AND ADMINISTRATION

• Hypotension associated with septic shock (2.2): (2)

o Dilute epinephrine in dextrose solution prior to infusion.
o Infuse epinephrine into a large vein.
o Titrate 0.05-2 mcg/kg/min to achieve desired blood pressure.
o Wean gradually. (2)

• Anaphylaxis:

- Administer intramuscularly or subcutaneously into anterolateral thigh every 5-10 minutes as needed
  o Adults and children over 30 kg (66 lb): 0.3-0.5 mg (0.3-0.5 mL)
  o Children under 30 kg (66 lb): 0.01 mg/kg (0.01 mL/kg)

• Intraocular surgery:

o Dilute 1 mL with 100 to 1000 mL of an ophthalmic irrigation fluid, for ophthalmic irrigation or intracameral injection. (2)

3 DOSAGE FORMS AND STRENGTHS

- Injection solution: 1 mg/1 mL, 2 mL single-use ampule. (3)

4 CONTRAINDICATIONS

None. (4)

5 WARNINGS AND PRECAUTIONS

- Monitor patient for acute severe hypertension. (5.1)
- Avoid extravasation into tissues, which can cause local necrosis. (5.2)
- Do not inject into buttocks, digits, hands, or feet. (5.3)
- Potential for pulmonary edema, which may be fatal. (5.4)
- May constrict renal blood vessels and decrease urine formation. (5.5)
- May induce potentially serious cardiac arrhythmias or aggravate angina pectoris, particularly in patients with underlying heart disease. (5.6)

6 ADVERSE REACTIONS

Most common adverse reactions to systemically administered epinephrine are headache; anxiety; apprehensiveness; restlessness; tremor; weakness; dizziness; sweating; palpitations; pallor; peripheral coldness; nausea/vomiting; and/or respiratory difficulties. Arrhythmias, including fatal ventricular fibrillation, rapid rises in blood pressure producing cerebral hemorrhage, and angina have occurred. (6.1, 6.2)

To report SUSPECTED ADVERSE REACTIONS, contact BPI Labs, LLC at (727) 471-0850 or FDA at 1-800-FDA-1088 or www.fda.gov/medwatch.

7 DRUG INTERACTIONS

- Drugs that counter the pressor effects of epinephrine include alpha blockers, vasodilators such as nitrates, diuretics, antihypertensives and ergot alkaloids. (7)
- Drugs that potentiate the effects of epinephrine include sympathomimetics, beta blockers, tricyclic antidepressants, MAO inhibitors, COMT inhibitors, clonidine, doxapram, oxytocin, levothyroxine sodium, and certain antihistamines. (7)
- Drugs that increase the arrhythmogenic potential of epinephrine include beta blockers, cyclopropane and halogenated hydrocarbon anesthetics, quinidine, antihistamines, exogenous thyroid hormones, diuretics, and cardiac glycosides. Observe for development of cardiac arrhythmias. (7)
- Potassium-depleting drugs, including corticosteroids, diuretics, and theophylline, potentiate the hypokalemic effects of epinephrine. (7)

8 USE IN SPECIFIC POPULATIONS

• Pregnancy: Epinephrine may lead to fetal anoxia, spotaneous abortion or both. (8.1)
• Elderly patients and pregnant women may be at greater risk of developing adverse reactions when epinephrine is administered parenterally. (8.1, 8.5)

See 17 for PATIENT COUNSELING INFORMATION

Revised: 02/2024

FULL PRESCRIBING INFORMATION

1 INDICATIONS AND USAGE

1.1 Hypotension associated with Septic Shock

Epinephrine Injection USP, 1 mg/mL is indicated to increase mean arterial blood pressure in adult patients with hypotension associated with septic shock.

1.2 Anaphylaxis

Emergency treatment of allergic reactions (Type I), including anaphylaxis, which may result from allergic reactions to insect stings, biting insects, foods, drugs, sera, diagnostic testing substances and other allergens, as well as idiopathic anaphylaxis or exercise-induced anaphylaxis. The signs and symptoms associated with anaphylaxis include flushing, apprehension, syncope, tachycardia, thready or unobtainable pulse associated with hypotension, convulsions, vomiting, diarrhea and abdominal cramps, involuntary voiding, airway swelling, laryngospasm, bronchospasm, pruritus, urticaria or angioedema, swelling of the eyelids, lips, and tongue.

1.3 Induction and Maintenance of Mydriasis during Intraocular Surgery

Induction and maintenance of mydriasis during intraocular surgery.

2 DOSAGE AND ADMINISTRATION

2.1 General Considerations

Inspect visually for particulate matter and discoloration prior to administration, whenever solution and container permit. Do not use if the solution is colored or cloudy, or if it contains particulate matter. Discard any unused portion.

2.2 Hypotension associated with Septic Shock

Dilute epinephrine in 5 percent dextrose solution or 5 percent dextrose and sodium chloride solution. These dextrose containing fluids provide protection against significant loss of potency by oxidation. Administration in saline solution alone is not recommended. Whole blood or plasma, if indicated to increase blood volume, should be administered separately.

Add 1 mL (1 mg) of epinephrine from its ampule to 1,000 mL of a 5 percent dextrose containing solution. Each mL of this dilution contains 1 mcg of epinephrine.

Correct blood volume depletion as fully as possible before any vasopressor is administered. When, as an emergency measure, intraaortic pressures must be maintained to prevent cerebral or coronary artery ischemia, epinephrine can be administered before and concurrently with blood volume replacement.

Whenever possible, give infusions of epinephrine into a large vein. Avoid using a catheter tie-in technique, because the obstruction to blood flow around the tubing may cause stasis and increased local concentration of the drug. Occlusive vascular diseases (for example, atherosclerosis, arteriosclerosis, diabetic endarteritis, Buerger's disease) are more likely to occur in the lower than in the upper extremity; therefore, avoid the veins of the leg in elderly patients or in those suffering from such disorders. There is potential for gangrene in a lower extremity when infusions of catecholamine are given in an ankle vein.

To provide hemodynamic support in septic shock associated hypotension in adult patients, the suggested dosing infusion rate of intravenously administered epinephrine is 0.05 mcg/kg/min to 2 mcg/kg/min, and is titrated to achieve a desired mean arterial pressure (MAP). The dosage may be adjusted periodically, such as every 10 to 15 minutes, in increments of 0.05 mcg/kg/min to 0.2 mcg/kg/min, to achieve the desired blood pressure goal.

Continuous epinephrine infusion is generally required over several hours or days until the patient's hemodynamic status improves. The duration of perfusion or total cumulative dose cannot be predicted.

After hemodynamic stabilization, wean incrementally over time, such as by decreasing doses of epinephrine every 30 minutes over a 12- to 24-hour period.

2.3 Anaphylaxis

Inject epinephrine intramuscularly or subcutaneously into the anterolateral aspect of the thigh, through clothing if necessary. When administering to a child, to minimize the risk of injection related injury, hold the leg firmly in place and limit movement prior to and during an injection. The injection may be repeated every 5 to 10 minutes as necessary. For intramuscular administration, use a needle long enough (at least 1/2 inch to 5/8 inch) to ensure the injection is administered into the muscle. Monitor the patient clinically for the severity of the allergic reaction and potential cardiac effects of the drug, with repeat doses titrated to effect. Do not administer repeated injections at the same site, as the resulting vasoconstriction may cause tissue necrosis.

Adults and Children 30 kg (66 lbs) or more: 0.3 to 0.5 mg (0.3 mL to 0.5 mL) of undiluted epinephrine administered intramuscularly or subcutaneously in the anterolateral aspect of the thigh, up to a maximum of 0.5 mg (0.5 mL) per injection, repeated every 5 to 10 minutes as necessary. Monitor clinically for reaction severity and cardiac effects.

Children less than 30 kg (66 lbs): 0.01 mg/kg (0.01 mL/kg) of undiluted epinephrine administered intramuscularly or subcutaneously in the anterolateral aspect of the thigh, up to a maximum of 0.3 mg (0.3 mL) per injection, repeated every 5 to 10 minutes as necessary. Monitor clinically for reaction severity and cardiac effects.

2.4 Induction and Maintenance of Mydriasis during Intraocular Surgery

Epinephrine must be diluted prior to intraocular use. Dilute 1 mL of epinephrine 1 mg/mL (1:1000) in 100 to 1000 mL of an ophthalmic irrigation fluid to create an epinephrine concentration of 1:100,000 to 1:1,000,000 (10 mcg/mL to 1 mcg/mL). Use the irrigating solution as needed for the surgical procedure.

After dilution in an ophthalmic irrigating fluid, epinephrine may also be injected intracamerally as a bolus dose of 0.1 mL at a dilution of 1:100,000 to 1:400,000 (10 mcg/mL to 2.5 mcg/mL).

3 DOSAGE FORMS AND STRENGTHS

Injection solution: 1 mg/1 mL epinephrine as a sterile solution in a 2 mL single-use clear glass ampule, marked Epinephrine Injection USP, 1 mg/mL.

4 CONTRAINDICATIONS

None.

5 WARNINGS AND PRECAUTIONS

5.1 Hypertension

When Epinephrine Injection is administered intravenously, titrate the infusion while monitoring vital signs. Invasive arterial blood pressure monitoring and central venous pressure monitoring are recommended. Because of varying response to epinephrine, dangerously high blood pressure may occur [see Drug Interactions (7)].

5.2 Extravasation and Tissue Necrosis with Intravenous Infusion

When Epinephrine Injection is administered intravenously, the infusion site should be checked frequently for free flow. Avoid extravasation of epinephrine into the tissues, to prevent local necrosis. Blanching along the course of the infused vein, sometimes without obvious extravasation, may be attributed to vasa vasorum constriction with increased permeability of the vein wall, permitting some leakage. This also may progress on rare occasions to superficial slough. Hence, if blanching occurs, consider changing the infusion site at intervals to allow the effects of local vasoconstriction to subside.

Antidote for Extravasation Ischemia: To prevent sloughing and necrosis in areas in which extravasation has taken place, infiltrate the area with 10 mL to 15 mL of saline solution containing from 5 mg to 10 mg of phentolamine, an adrenergic blocking agent. Use a syringe with a fine hypodermic needle, with the solution being infiltrated liberally throughout the area, which is easily identified by its cold, hard, and pallid appearance. Sympathetic blockade with phentolamine causes immediate and conspicuous local hyperemic changes if the area is infiltrated within 12 hours.

5.3 Incorrect Locations of Injection for Anaphylaxis

When Epinephrine Injection is used for the treatment of anaphylaxis, the most appropriate location for administration is into the anterolateral aspect of the thigh (vastus lateralis muscle) because of its location, size, and available blood flow. Injection into (or near) smaller muscles, such as in the deltoid, is not recommended due to possible differences in absorption associated with this use.

Do not administer repeated injections of epinephrine at the same site, as the resulting vasoconstriction may cause tissue necrosis.

Do not inject into buttock. Injection into the buttock may not provide effective treatment of anaphylaxis and has been associated with the development of Clostridial infections (gas gangrene). Cleansing with alcohol does not kill bacterial spores, and therefore, does not lower this risk.

Do not inject into digits, hands, or feet. Epinephrine is a strong vasoconstrictor. Accidental injection into the digits, hands or feet may result in loss of blood flow to the affected area and has been associated with tissue necrosis.

5.4 Pulmonary Edema

When Epinephrine Injection is administered intravenously, there is risk of pulmonary edema because of the peripheral constriction and cardiac stimulation produced. Treatment of pulmonary edema consists of a rapidly acting alpha-adrenergic blocking drug (such as phentolamine mesylate) and respiratory support.

5.5 Renal Impairment

Intravenously administered epinephrine initially may produce constriction of renal blood vessels and decrease urine formation.

5.6 Cardiac Arrhythmias and Ischemia

Epinephrine may induce cardiac arrhythmias and angina pectoris in patients, especially patients suffering from coronary artery disease, organic heart disease, cerebrovascular disease, hypertension, or patients who are receiving drugs that sensitize the myocardium [see Adverse Reactions (6) and Drug Interactions (7)]. Treatment of arrhythmias consists of administration of a beta-adrenergic blocking drug (such as propranolol).

5.7 Injury with Undiluted Intraocular Solution

Epinephrine must be diluted before intraocular use. Other epinephrine products that contain sodium bisulfite have been associated with corneal endothelial damage when used in the eye at undiluted concentrations (1 mg/mL). Although this Epinephrine product contains no sulfites or preservatives, warning is still advised [see Dosage and Administration (2.4)].

5.8 Serious Infections at the Injection Site

Rare cases of serious skin and soft tissue infections, including necrotizing fasciitis and myonecrosis caused by Clostridia (gas gangrene), have been reported at the injection site following epinephrine injection for anaphylaxis. Clostridium spores can be present on the skin and introduced into the deep tissue with subcutaneous or intramuscular injection. While cleansing with alcohol may reduce presence of bacteria on the skin, alcohol cleansing does not kill Clostridium spores. To decrease the risk of Clostridium infection, do not inject Epinephrine Injection into the buttock [see Warnings and Precautions (5.3)]. Advise patients to seek medical care if they develop signs or symptoms of infection, such as persistent redness, warmth, swelling, or tenderness, at the epinephrine injection site.

5.9 Other Disease Interactions

Epinephrine should be administered with caution to patients with hyperthyroidism, Parkinson’s disease, diabetes mellitus, pheochromocytoma, elderly individuals, and pregnant women. Patients with Parkinson’s disease may experience psychomotor agitation or notice a temporary worsening of symptoms. Diabetic patients may experience transient increases in blood sugar. Despite these concerns, the presence of these conditions is not a contraindication to epinephrine administration in an acute, life-threatening situation.

6 ADVERSE REACTIONS

6.1 Adverse Reactions associated with Epinephrine Infusion (for Hypotension associated with Septic Shock)

The following adverse reactions associated with the infusion of epinephrine were identified in the literature. Because these reactions are reported voluntarily from a population of uncertain size, it is not always possible to estimate their frequency reliably or to establish a causal relationship to drug exposure.

Cardiovascular disorders: tachycardia, supraventricular tachycardia, ventricular arrhythmias, myocardial ischemia, myocardial infarction, limb ischemia, pulmonary edema

Gastrointestinal disorders: Nausea, vomiting

General disorders and administrative site conditions: Chest pain, extravasation,

Metabolic: hypoglycemia, hyperglycemia, insulin resistance, hypokalemia, lactic acidosis

Nervous system disorders: Headache, nervousness, paresthesia, tremor, stroke, central nervous system bleeding

Psychiatric disorders: Excitability

Renal disorders: Renal insufficiency

Respiratory: Pulmonary edema, rales

Skin and subcutaneous tissue disorders: Diaphoresis, pallor, piloerection, skin blanching, skin necrosis with extravasation

6.2 Adverse Reactions associated with Intramuscular or Subcutaneous Use (for Anaphylaxis)

Common adverse reactions to systemically administered epinephrine include anxiety, apprehensiveness, restlessness, tremor, weakness, dizziness, sweating, palpitations, pallor, nausea and vomiting, headache, and respiratory difficulties. These symptoms occur in some persons receiving therapeutic doses of epinephrine, but are more likely to occur in patients with heart disease, hypertension, or hyperthyroidism [see Warnings and Precautions (5.9)].

Due to the lack of randomized, controlled clinical trials of epinephrine for the treatment of anaphylaxis, the true incidence of adverse reactions associated with the systemic use of epinephrine is difficult to determine. Adverse reactions reported in observational trials, case reports, and studies are listed below by body system:

Cardiovascular[see Warnings and Precautions (5.6)]: angina, arrhythmias, hypertension, pallor, palpitations, tachyarrhythmia, tachycardia, vasoconstriction, and ventricular ectopy. Angina may occur in patients with coronary artery disease. Arrhythmias, including fatal ventricular fibrillation, have occurred, particularly in patients with underlying organic heart disease or patients receiving drugs that sensitize the heart to arrhythmias. Rapid rises in blood pressure associated with epinephrine use have produced cerebral hemorrhage, particularly in elderly patients with cardiovascular disease.

Respiratory: respiratory difficulties.

Neurological: dizziness, disorientation, excitability, headache, impaired memory, lightheadedness, nervousness, panic, psychomotor agitation, sleepiness, tingling, tremor, and weakness.

Psychiatric: anxiety, apprehensiveness, restlessness.

Gastrointestinal: nausea, vomiting.

Skin: sweating.

Other: Patients with Parkinson’s disease may experience psychomotor agitation or a temporary worsening of symptoms [see Warnings and Precautions (5.9)]. Diabetic patients may experience transient increases in blood sugar [see Warnings and Precautions (5.9)].

Accidental injection into the digits, hands or feet may result in loss of blood flow to the affected area [see Warnings and Precautions (5.3)]. Adverse events experienced as a result of an injection into these areas include increased heart rate, local reactions including injection site pallor, coldness, hypoesthesia, and tissue loss, or injury at the injection site resulting in bruising, bleeding, discoloration, erythema, and skeletal injury.

Injection into the buttock has resulted in cases of gas gangrene [see Warnings and Precautions (5.3)].

Rare cases of serious skin and soft tissue infections, including necrotizing fasciitis and myonecrosis caused by Clostridia (gas gangrene), have been reported following epinephrine injection in the thigh [see Warnings and Precautions (5.8)].

6.3 Adverse Reactions Associated with Intraocular Use (for Mydriasis)

Epinephrine products containing sodium bisulfite have been associated with corneal endothelial damage when used in the eye at undiluted concentrations (1 mg/mL). Although this Epinephrine product contains no sulfites or preservatives, warning is still advised [see Warnings and Precautions (5.7)].

7 DRUG INTERACTIONS

Drugs antagonizing pressor effects of epinephrine

- α-blockers, such as phentolamine
- Vasodilators, such as nitrates
- Diuretics
- Antihypertensives
- Ergot alkaloids

Drugs potentiating pressor effects of epinephrine

- Sympathomimetics
- β-blockers, such as propranolol
- Tricyclic anti-depressants
- Monoamine oxidase (MAO) inhibitors
- Catechol-O-methyl transferase (COMT) inhibitors, such as entacapone
- Clonidine
- Doxapram
- Oxytocin
- Drugs potentiating arrhythmogenic effects of epinephrine. Patients who are concomitantly receiving any of the following drugs should be observed carefully for the development of cardiac arrhythmias [see Warnings and Precautions (5.6) and Adverse Reactions (6)].
- β-blockers, such as propranolol
- Cyclopropane or halogenated hydrocarbon anesthetics, such as halothane
- Antihistamines
- Thyroid hormones
- Diuretics
- Cardiac glycosides, such as digitalis glycosides
- Quinidine

Drugs potentiating hypokalemic effects of epinephrine

- Potassium depleting diuretics
- Corticosteroids
- Theophylline

Epinephrine should not be used to counteract circulatory collapse or hypotension caused by phenothiazines, as a reversal of the pressor effects of epinephrine may result in further lowering of blood pressure.

Epinephrine may antagonize the neuronal blockade produced by guanethidine resulting in decreased antihypertensive effect and requiring increased dosage of the latter.

8 USE IN SPECIFIC POPULATIONS

8.1 Pregnancy

Risk Summary

Prolonged experience with epinephrine use in pregnant women over several decades, based on published literature, does not identify a drug-associated risk of major birth defects, miscarriage, or adverse maternal or fetal outcomes.
However, there are risks to the mother and fetus associated with epinephrine use during labor and delivery (see Clincial Considerations). In animal reproduction studies, epinephrine administered by the subcutaneous route to pregnant rabbits, mice, and hamsters, during the period of organogenesis, resulted in adverse developmental effects (including gastroschisis, embryonic lethality, and delayed skeletal ossification) at doses approximately 2 times the maximum recommended daily intramuscular, subcutaneous, or intravenous dose (see Data).

The estimated background risk of major birth defects and miscarriage for the indicated population is unknown. All pregnancies have a background risk of birth defect, loss, or other adverse outcomes. In the United States general population, the estimated background risk of major birth defects and miscarriage in clinically recognized pregnancies is 2 to 4% and 15 to 20%, respectively.

Clinical Considerations

Disease-associated maternal and/or embryo/fetal risk

During pregnancy, anaphylaxis can be catastrophic and can lead to hypoxicischemic encephalopathy and permanent central nervous system damage or death in the mother and, more commonly, in the fetus or neonate. The prevalence of anaphylaxis occurring during pregnancy is reported to be approximately 3 cases per 100,000 deliveries.

Management of anaphylaxis during pregnancy is similar to managment in the general population. Epinephrine is the first line-medication of choice for treatment of anaphylaxis; it should be used in the same manner in pregnant and non-pregnant patients. In conjunction with the administration of epinephrine, the patient should seek immediate medical or hospital care.

Hypotension associated with septic shock is a medical emergency in pregnancy which can be fatal if left untreated. Delaying treatment in pregnany women with hypotension associated with septic shock may increase the risk of maternal and fetal morbidity and mortality. Life-sustaining therapy for the pregnany woman should not be withheld due to potential concerns regarding the effects of epinephrine on the fetus.

Labor or Delivery

Epinephrine usually inhibits spontaneous or oxytocin-induced contractions of the pregnant human uterus and may delay the second stage of labor. Avoid epinephrine during the second stage of labor. In dosage sufficient to reduce uterine contractions, the drug may cause a prolonged period of uterine atony with hemorrhage. Avoid epinephrine in obstetrics when maternal blood pressure exceeds 130/80 mmHg.

Although epinephrine may improve maternal hypotension associated with septic shock and anaphylaxis, it may result in uterine vasoconstriction, decreased uterine blood flow, and fetal anoxia.

Data

Animal Data

In an embryofetal development study with pregnany rabbits dosed during the period of organogenesis (on days 3 to 5, 6 to 7, or 7 to 9 of gestation), epinephrine caused teratogenic effects (including gastroschisis) at doses approximately 15 times the maximum recommended intramuscular, subcutaneous, or intravenous dose (on a mg/m2 basis at a maternal subcutaneous dose of 1.2 mg/kg/day for 2 to 3 days). Animals treated on days 6 to 7 had decreased number of implantations.

In an embryofetal development study, pregnant mice were administered epinephrine (0.1 to 10 mg/kg/day) on Gestation Days 6 to 15. Teratogenic effects, embryonic lethality, and delays in skeletal ossification were observed at approximately 3 times the maximum recommended intramuscular, subcutaneous, or intravenous dose (on a mg/m^2 basis at maternal subcutaneous dose of 1 mg/kg/day for 10 days). These effects were not seen in mice at approximately 2 times the maximum recommended daily intramuscular or subcutaneous dose (on a mg/m^2 basis at a subcutaneous maternal dose of 0.5 mg/kg/day for 10 days).

In an embryofetal development study with pregnant hamsters dosed during the period of organogenesis from gestation days 7 to 10, epinephrine produced reductions in litter size and delayed skeletal ossification at doses approximately 2 times the maximum recommended intramuscular, subcutaneous, or intravenous dose (on a mg/m^2 basis at a maternal subcutaneous dose of 0.5 mg/kg/day).

8.2 Lactation

Risk Summary

There is not information regarding the presence of epinephrine in human milk or the effects of epinephrine on the breastfed infant or on milk production. However, due to its poor oral bioavailability and short half-life, epinephrine exposure is expected to be very low in the breastfed infant.

Epinephrine is the first-line medication of choice for treatment of anaphylaxis; it should be used in the same manner for anaphylaxis in breastfeeding and non-breastfeeding patients.

8.4 Pediatric Use

Safety and effectiveness of epinephrine in pediatric patients with septic shock have not been established.

Clinical use data support weight-based dosing for treatment of anaphylaxis in pediatric patients, and other reported clinical experience with the use of epinephrine suggests that the adverse reactions seen in children are similar in nature and extent to those both expected and reported in adults.

The safety and effectiveness of epinephrine (at a dilution of 1:100,000 to 1:400,000) for induction and maintenance of mydriasis during intraocular surgery have been established in pediatric patients. Use of epinephrine for induction and maintenance of mydriasis during intraocular surgery in pediatric patients is supported by adequate and well controlled studies in adults and uncontrolled studies in pediatric patients.

8.5 Geriatric Use

Clinical studies of epinephrine for the treatment of hypotension associated with septic shock did not include sufficient numbers of subjects aged 65 and over to determine whether they respond differently from younger subjects. Other reported clinical experience has not identified differences in responses between the elderly and younger patients. In general, dose selection for an elderly patient should be cautious, usually starting at the low end of the dosing range, reflecting the greater frequency of decreased hepatic, renal, or cardiac function, and of concomitant disease or other drug therapy.

Clinical studies for the treatment of anaphylaxis have not been performed in subjects aged 65 and over to determine whether they respond differently from younger subjects. However, other reported clinical experience with use of epinephrine for the treatment of anaphylaxis has identified that geriatric patients may be particularly sensitive to the effects of epinephrine. Therefore, for the treatment of anaphylaxis, consider starting with a lower dose to take into account potential concomitant disease or other drug therapy.

For induction and maintenance of mydriasis during intraocular surgery, no overall differences have been observed between elderly and other patients.

10 OVERDOSAGE

Overdosage of epinephrine may produce extremely elevated arterial pressure, which may result in cerebrovascular hemorrhage, particularly in elderly patients. Overdosage may also result in pulmonary edema because of peripheral vascular constriction together with cardiac stimulation. Epinephrine overdosage may also cause transient bradycardia followed by tachycardia and these may be accompanied by potentially fatal cardiac arrhythmias. Premature ventricular contractions may appear within one minute after injection and may be followed by multifocal ventricular tachycardia (prefibrillation rhythm). Subsidence of the ventricular effects may be followed by atrial tachycardia and occasionally by atrioventricular block. Myocardial ischemia and infarction, cardiomyopathy, extreme pallor and coldness of the skin, metabolic acidosis due to elevated blood lactic acid levels, and renal insufficiency and failure have also been reported.

Epinephrine is rapidly inactivated in the body and treatment following overdose is primarily supportive. Treatment of pulmonary edema consists of a rapidly acting alpha-adrenergic blocking drug (such as phentolamine mesylate) and respiratory support. Treatment of arrhythmias consists of administration of a beta-adrenergic blocking drug (such as propranolol). If necessary, pressor effects may be counteracted by rapidly acting vasodilators (such as nitrites) or alpha-adrenergic blocking drugs. If prolonged hypotension follows such measures, it may be necessary to administer another pressor drug.

11 DESCRIPTION

Epinephrine Injection USP, 1 mg/mL is supplied as a sterile aqueous solution with a pH range of 2.2-5.0, that is colorless and nonpyrogenic. Each milliliter contains 1 mg epinephrine, sodium chloride 8.6 mg (for isotonicity), hydrochloric acid for pH adjustment, and water for injection, USP, qs. Contains no preservatives or sulfites.

Solution must be diluted prior to intravenous or ocular use.

Epinephrine, USP is a sympathomimetic catecholamine (adrenergic agent) designated chemically as 4-[1-hydroxy-2 (methylamino) ethyl]-1,2 benzenediol, a white, microcrystalline powder. It has the following structural formula:

The molecular weight of epinephrine is 183.2.

Epinephrine solution deteriorates rapidly on exposure to air or light, turning pink from oxidation to adrenochrome and brown from the formation of melanin.

12 CLINICAL PHARMACOLOGY

12.1 Mechanism of Action

Epinephrine acts on both alpha (α)- and beta (β)-adrenergic receptors. The mechanism of the rise in blood pressure is 3-fold: a direct myocardial stimulation that increases the strength of ventricular contraction (positive inotropic action), an increased heart rate (positive chronotropic action), and peripheral vasoconstriction.

12.2 Pharmacodynamics

Intravenous use for hypotension associated with septic shock:

Following intravenous administration of epinephrine, increases in systolic blood pressure and heart rate are observed. Decreases in systemic vascular resistance and diastolic blood pressure are observed at low doses of epinephrine because of β2-mediated vasodilation, but are overtaken by α1-mediated peripheral vasoconstriction at higher doses leading to increase in diastolic blood pressure. The onset of blood pressure increase following an intravenous dose of epinephrine is < 5 minutes and the time to offset blood pressure response occurs within 20 min. Most vascular beds are constricted including renal, splanchnic, mucosal and skin.

Intramuscular and subcutaneous use for anaphylaxis

Through its action on alpha-adrenergic receptors, epinephrine lessens the vasodilation and increased vascular permeability that occurs during anaphylaxis, which can lead to loss of intravascular fluid volume and hypotension.

Through its action on beta-adrenergic receptors, epinephrine causes bronchial smooth muscle relaxation and helps alleviate bronchospasm, wheezing and dyspnea that may occur during anaphylaxis.

Epinephrine also alleviates pruritus, urticaria, and angioedema and may relieve gastrointestinal and genitourinary symptoms associated with anaphylaxis because of its relaxer effects on the smooth muscle of the stomach, intestine, uterus and urinary bladder.

Epinephrine increases glycogenolysis, reduces glucose up take by tissues, and inhibits insulin release in the pancreas, resulting in hyperglycemia and increased blood lactic acid [see Warnings and Precautions (5.9)].

Intraocular use for mydriasis

Epinephrine causes mydriasis when administered intraocularly or parenterally.

12.3 Pharmacokinetics

When administered parenterally or intraocularly, epinephrine has a rapid onset and short duration of action.

Following intravenous injection, epinephrine is rapidly cleared from the plasma with an effective half-life of < 5 min. A pharmacokinetic steady state following continuous intravenous infusion is achieved within 10-15 min. In patients with septic shock, epinephrine displays dose-proportional pharmacokinetics in the infusion dose range of 0.03 to 1.7 mcg/kg/min.

The extent of human systemic exposure at the labeled intraocular dose has not been evaluated, however, significant systemic concentrations or plasma exposure of epinephrine are not expected when administered intraocularly.

Epinephrine is extensively metabolized with only a small amount excreted unchanged.

Epinephrine is rapidly degraded to vanillylmandelic acid, an inactive metabolite, by monoamine oxidase and catechol-O-methyltransferase that are abundantly expressed in the liver, kidneys and other extraneuronal tissues. The tissues with the highest contribution to removal of circulating exogenous epinephrine are the liver (32%), kidneys (25%), skeletal muscle (20%), and mesenteric organs (12%).

Special Populations

Elderly

In a pharmacokinetic study of 45-minute epinephrine infusions given to healthy men aged 20 to 25 years and healthy men aged 60 to 65 years, the mean plasma metabolic clearance rate of epinephrine at steady state was greater among the older men (144.8 versus 78 mL/kg/min for a 14.3 ng/kg/min infusion).

Body Weight

Body weight has been found to influence epinephrine pharmacokinetics. Higher body weight was associated with a higher plasma epinephrine clearance and a lower concentration plateau.

13 NONCLINICAL TOXICOLOGY

13.1 Carcinogenesis, Mutagenesis, Impairment of Fertility

Long-term studies to evaluate the carcinogenic potential of epinephrine have not been conducted.

Epinephrine and other catecholamines have been shown to have mutagenic potential in vitro. Epinephrine was positive in the Salmonella bacterial reverse mutation assay, positive in the mouse lymphoma assay, and negative in the in vivo micronucleus assay. Epinephrine is an oxidative mutagen based on the E. coli WP2 Mutoxitest bacterial reverse mutation assay. This should not prevent the use of epinephrine under the conditions noted under the Indications and Usage.

The potential for epinephrine to impair reproductive performance has not been evaluated, but epinephrine has been shown to decrease implantation in female rabbits dosed subcutaneously with 1.2 mg/kg/day (15-fold the highest human intramuscular or subcutaneous daily dose) during gestation days 3 to 9.

13.2 Animal Toxicology and/or Pharmacology

Epinephrine was associated with metabolic effects, decreased mesentery, coronary and renal conductance in a sheep model of septic shock. Data from hemolysis study have shown that epinephrine at 1:1000 dilution is non-hemolytic. Epinephrine infusion significantly increased the MAP (69 vs. 86 mmHg) and cardiac output (6.4 vs. 7.1 L/min) and decreased renal blood flow (330 vs. 247 mL/min).

14 CLINICAL STUDIES

14.1 Hypotension associated with Septic Shock

Fourteen clinical studies from the literature documented that epinephrine increases the mean arterial pressure (MAP) in patients with hypotension associated with septic shock.

14.2 Induction and Maintenance of Mydriasis during Intraocular Surgery

In randomized, controlled studies, patients undergoing routine cataract extraction were evaluated after receiving intraocular irrigation with or without epinephrine diluted up to 1:1,666,666 (0.6 mcg/mL). Patients have also been evaluated after receiving bolus intracameral injections of epinephrine diluted between 1:25,000 (40 mcg/mL) and 1:400,000 (2.5 mcg/mL).

In patients with similar pupil diameters at baseline, with or without the use of preoperative mydriatic agents, mydriasis was maintained better in the eyes receiving epinephrine by an average of one to two millimeters in pupil diameter.

Pupil constriction to 5 mm or less occurred more often in the patients not receiving epinephrine.

Mean pulse rate and blood pressure showed no significance difference between patients receiving epinephrine and controls and there was no increased incidence of ventricular dysrhythmias in patients receiving epinephrine.

16 HOW SUPPLIED/STORAGE AND HANDLING

Epinephrine Injection USP, 1 mg/mL is a sterile solution containing 1 mg/1 mL epinephrine in a 2 mL clear glass ampule. Supplied in a box of 10 single-use ampules (NDC 54288-103-10).

Epinephrine is light sensitive. Protect from light until ready to use.

Do not refrigerate. Protect from freezing.

Store at room temperature, between 20° to 25°C (68° to 77°F). (See USP Controlled Room Temperature.) Protect from alkalis and oxidizing agents.

Inspect visually for particulate matter and discoloration prior to administration. Do not use the solution if it is colored or cloudy, or if it contains particulate matter.

Product repackaged by: Henry Schein, Inc., Bastian, VA 24314
From Original Manufacturer/Distributor's NDC and Unit of Sale | To Henry Schein Repackaged Product NDC and Unit of Sale | Total Strength/Total Volume (Concentration) per unit
NDC 54288-103-10 10 2 mL single-use ampules in a box | NDC 0404-9857-01 1 2 mL single-use ampule in a bag (Vial bears NDC 54288-103-10) | 1 mg/1 mL

17 PATIENT COUSELING INFORMATION

Advise patients or their caregivers about common adverse reactions associated with the use of epinephrine, including an increase in heart rate, the sensation of a more forceful heartbeat, palpitations, sweating, nausea and vomiting, difficulty breathing, pallor, dizziness, weakness or shakiness, headache, apprehension, nervousness, or anxiety. These symptoms and signs usually subside rapidly, especially with rest, quiet and recumbent positioning.

Warn patients with a good response to initial treatment about the possibility of recurrence of anaphylaxis symptoms and instruct patients to obtain medical attention if symptoms return.

Advise patients with diabetes that they may develop increased blood glucose levels following epinephrine administration.

Rare cases of serious skin and soft tissue infections, including necrotizing fasciitis and myonecrosis caused by Clostridia (gas gangrene), have been reported at the injection site following epinephrine injection for anaphylaxis. Advise patients to seek medical care if they develop signs or symptoms of infection, such as persistent redness, warmth, swelling, or tenderness, at the epinephrine injection site[see Warnings and Precautions (5.8)].

Revised: February 2024 LI04I R-2402

Manufactured for:

BPI Labs, LLC

12393 Belcher Rd S, Suite 450

Largo, FL 33773

USA

Manufactured by:

Sintetica SA
Via Penate 5
6850 Mendrisio, Switzerland